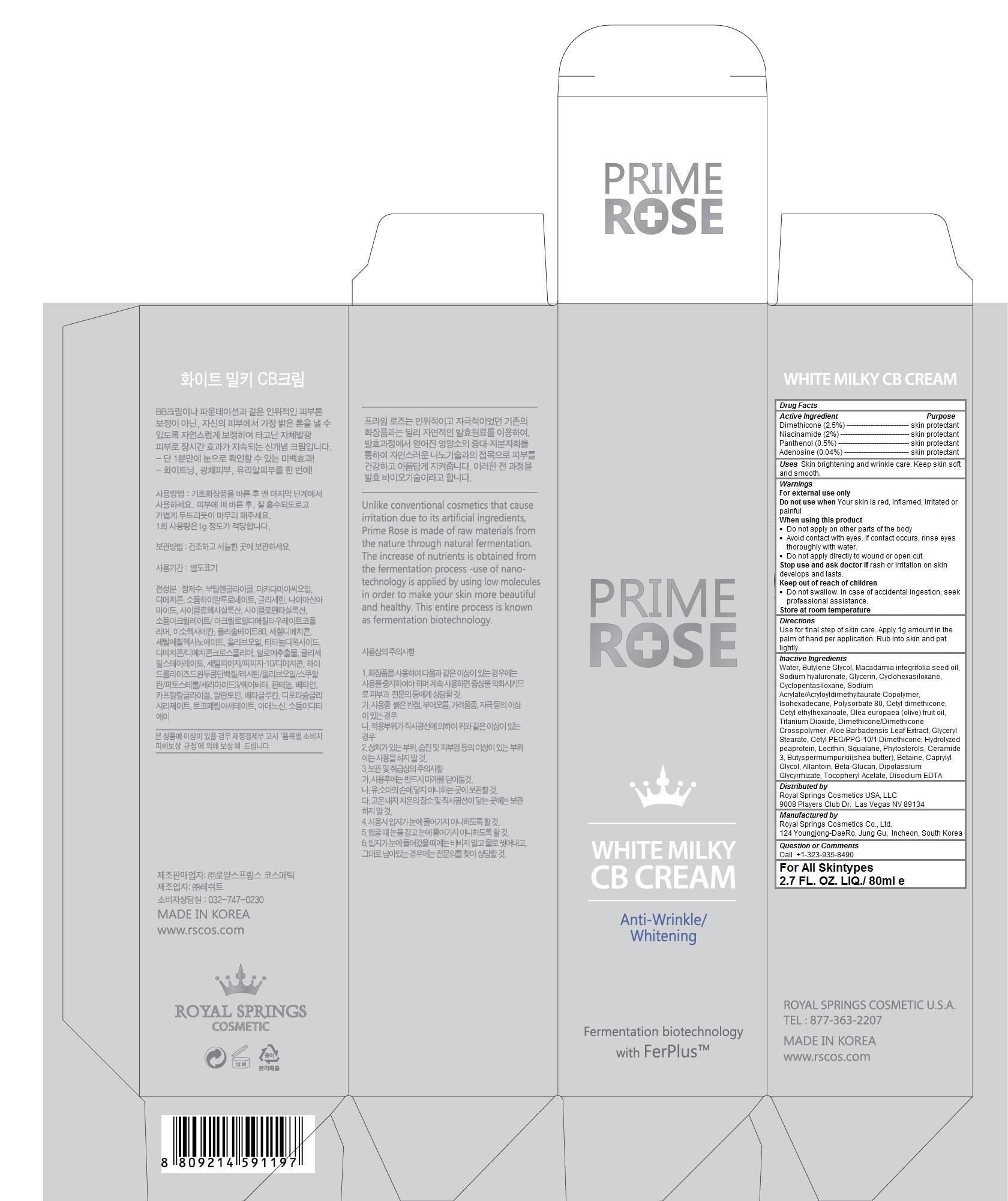 DRUG LABEL: PRIMEROSE WHITE MILKY CB
NDC: 69888-103 | Form: CREAM
Manufacturer: Royal Springs Cosmetics USA, LLC
Category: otc | Type: HUMAN OTC DRUG LABEL
Date: 20190115

ACTIVE INGREDIENTS: DIMETHICONE 0.025 1/80 mL; NIACINAMIDE 0.02 1/80 mL; PANTHENOL 0.005 1/80 mL; ADENOSINE 0.0004 1/80 mL
INACTIVE INGREDIENTS: WATER; BUTYLENE GLYCOL; MACADAMIA OIL; HYALURONATE SODIUM; GLYCERIN; CYCLOMETHICONE 6; CYCLOMETHICONE 5; ISOHEXADECANE; POLYSORBATE 80; CETYL DIMETHICONE 45; CETYL ETHYLHEXANOATE; OLIVE OIL; TITANIUM DIOXIDE; DIMETHICONE CROSSPOLYMER (450000 MPA.S AT 12% IN CYCLOPENTASILOXANE); ALOE VERA LEAF; GLYCERYL MONOSTEARATE; CETYL PEG/PPG-10/1 DIMETHICONE (HLB 2); EGG PHOSPHOLIPIDS; SQUALANE; CERAMIDE 3; SHEA BUTTER; BETAINE; CAPRYLYL GLYCOL; ALLANTOIN; GLYCYRRHIZINATE DIPOTASSIUM; .ALPHA.-TOCOPHEROL ACETATE; EDETATE DISODIUM

PRIMEROSE WHITE MILKY CB CREAM

Active ingredients

Dimethicone (2.5%)
Niacinamide (2%)
Panthenol (0.5%)
Adenosine (0.04%)

Purpose

skin protectant

Keep out of reach of children

- Do not swallow. In case of accidental ingestion, seek professional assistance.

Uses

Skin brightening and wrinkle care. Keep skin soft and smooth.

Warnings

For external use only
Do not use when Your skin is red, inflamed, irritated or painful
When using this product
- Do not apply on other parts of the body
- Avoid contact with eyes. If contact occurs, rinse eyes thoroughly with water.
- Do not apply directly to wound or open cut.
Stop use and ask doctor if rash or irritation on skin develops and lasts.
Store at room temperature

Directions

Use for final step of skin care. Apply 1g amount in the palm of hand per application. Rub into skin and pat lightly.

Inactive ingredients

Water, Butylene Glycol, Macadamia integrifolia seed oil, Sodium hyaluronate, Glycerin, Cyclohexasiloxane, Cyclopentasiloxane, Sodium Acrylate/Acryloyldimethyltaurate Copolymer, Isohexadecane, Polysorbate 80, Cetyl dimethicone, Cetyl ethylhexanoate, Olea europaea (olive) fruit oil, Titanium Dioxide, Dimethicone/Dimethicone Crosspolymer, Aloe Barbadensis Leaf Extract, Glyceryl Stearate, Cetyl PEG/PPG-10/1 Dimethicone, Hydrolyzed peaprotein, Lecithin, Squalane, Phytosterols, Ceramide 3, Butyspermumpurkii(shea butter), Betaine, Caprylyl Glycol, Allantoin, Beta-Glucan, Dipotassium Glycyrrhizate, Tocopheryl Acetate, Disodium EDTA